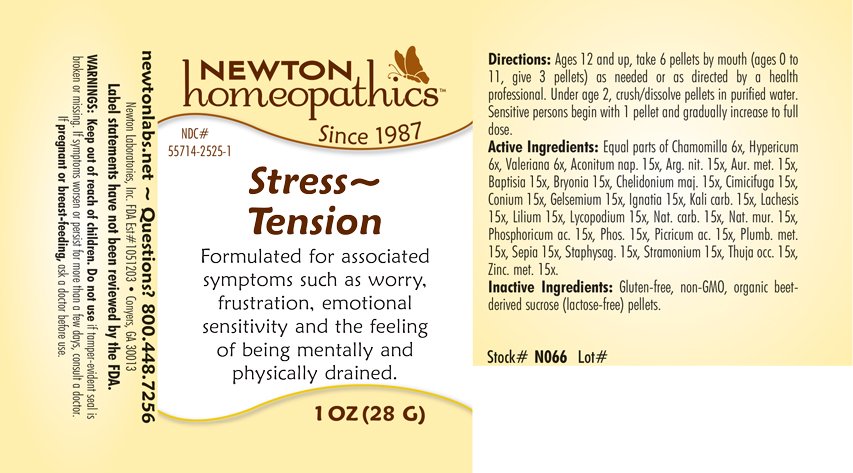 DRUG LABEL: Stress-Tension
NDC: 55714-2525 | Form: PELLET
Manufacturer: Newton Laboratories, Inc.
Category: homeopathic | Type: HUMAN OTC DRUG LABEL
Date: 20250210

ACTIVE INGREDIENTS: VALERIAN 6 [hp_X]/1 g; ZINC 15 [hp_X]/1 g; MATRICARIA CHAMOMILLA 6 [hp_X]/1 g; ACONITUM NAPELLUS 15 [hp_X]/1 g; SILVER NITRATE 15 [hp_X]/1 g; GOLD 15 [hp_X]/1 g; BAPTISIA TINCTORIA ROOT 15 [hp_X]/1 g; BRYONIA ALBA ROOT 15 [hp_X]/1 g; CHELIDONIUM MAJUS 15 [hp_X]/1 g; BLACK COHOSH 15 [hp_X]/1 g; CONIUM MACULATUM FLOWERING TOP 15 [hp_X]/1 g; GELSEMIUM SEMPERVIRENS ROOT 15 [hp_X]/1 g; STRYCHNOS IGNATII SEED 15 [hp_X]/1 g; POTASSIUM CARBONATE 15 [hp_X]/1 g; LACHESIS MUTA VENOM 15 [hp_X]/1 g; LILIUM LANCIFOLIUM WHOLE FLOWERING 15 [hp_X]/1 g; LYCOPODIUM CLAVATUM SPORE 15 [hp_X]/1 g; SODIUM CARBONATE 15 [hp_X]/1 g; SODIUM CHLORIDE 15 [hp_X]/1 g; PHOSPHORIC ACID 15 [hp_X]/1 g; PHOSPHORUS 15 [hp_X]/1 g; PICRIC ACID 15 [hp_X]/1 g; LEAD 15 [hp_X]/1 g; SEPIA OFFICINALIS JUICE 15 [hp_X]/1 g; DELPHINIUM STAPHISAGRIA SEED 15 [hp_X]/1 g; DATURA STRAMONIUM 15 [hp_X]/1 g; THUJA OCCIDENTALIS LEAFY TWIG 15 [hp_X]/1 g; HYPERICUM PERFORATUM 6 [hp_X]/1 g
INACTIVE INGREDIENTS: SUCROSE

Stress 2525P

INDICATIONS & USAGE SECTION

Formulated for associated symptoms such as worry, frustration, emotional sensitivity and the feeling of being mentally and physically drained.

DOSAGE & ADMINISTRATION SECTION

Directions: Ages 12 and up, take 6 pellets by mouth (ages 0 to 11, give 3 pellets) as needed or as directed by a health professional. Under age 2, crush/dissolve pellets in purified water. Sensitive persons begin with 1 pellet and gradually increase to full dose.

OTC - ACTIVE INGREDIENT SECTION

Equal parts of Chamomilla 6x, Hypericum perforatum 6x, Valeriana officinalis 6x, Aconitum napellus 15x, Argentum nitricum 15x, Aurum metallicum 15x, Baptisia 15x, Bryonia 15x, Chelidonium majus 15x, Cimicifuga racemosa 15x, Conium maculatum 15x, Gelsemium sempervirens 15x, Ignatia amara 15x, Kali carbonicum 15x, Lachesis mutus 15x, Lilium tigrinum 15x, Lycopodium clavatum 15x, Natrum carbonicum 15x, Natrum muriaticum 15x, Phosphoricum acidum 15x, Phosphorus 15x, Picricum acidum 15x, Plumbum metallicum 15x, Sepia 15x, Staphysagria 15x, Stramonium 15x, Thuja occidentalis 15x, Zincum metallicum 15x.

OTC - PURPOSE SECTION

Formulated for associated symptoms such as worry, frustration, emotional sensitivity and the feeling of being mentally and physically drained.

INACTIVE INGREDIENT SECTION

Inactive Ingredients: Gluten-free, non-GMO, organic beet-derived sucrose (lactose-free) pellets.

QUESTIONS SECTION

newtonlabs.net - Questions? 800.448.7256

Newton Laboratories, Inc. FDA Est # 1051203 Conyers, GA 30013

WARNINGS SECTION

WARNINGS: Keep out of reach of children. Do not use if tamper-evident seal is broken or missing. If symptoms worsen or persist for more than a few days, consult a doctor. If pregnant or breast-feeding, ask a doctor before use.

OTC - PREGNANCY OR BREAST FEEDING SECTION

If pregnant or breast-feeding, ask a doctor before use.

OTC - KEEP OUT OF REACH OF CHILDREN SECTION

Keep out of reach of children.